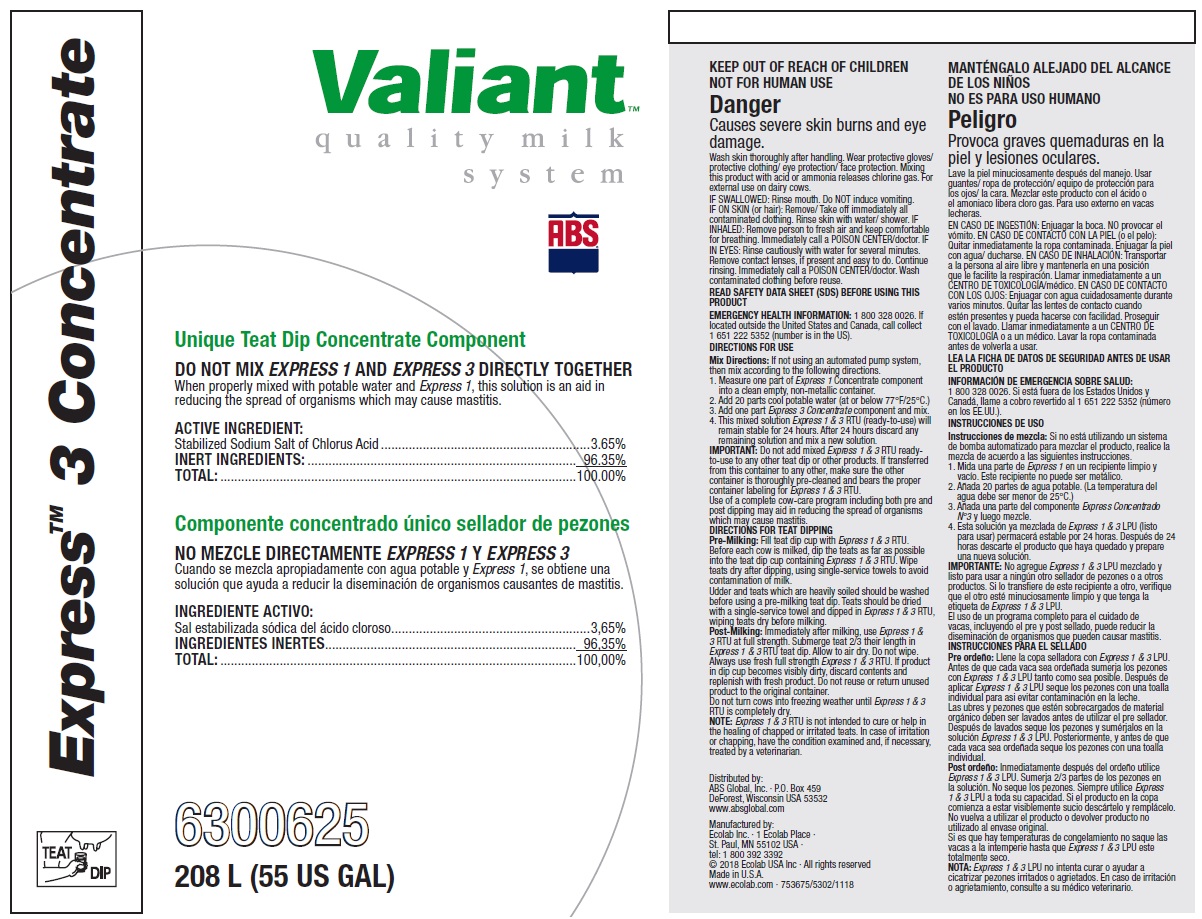 DRUG LABEL: ABS Express 3 Concentrate
NDC: 59282-104 | Form: SOLUTION
Manufacturer: ABS Global Inc.
Category: animal | Type: OTC ANIMAL DRUG LABEL
Date: 20230726

ACTIVE INGREDIENTS: SODIUM CHLORITE 36.5 mg/1 mL
INACTIVE INGREDIENTS: WATER

KEEP OUT OF REACH OF CHILDREN

NOT FOR HUMAN USE

Danger

Causes severe skin burns and eye damage.

Wash skin thoroughly after handling. Wear protective gloves/ protective clothing/ eye protection/ face protection. Mixing this product with acid or ammonia releases chlorine gas. For external use on dairy cows.

VETERINARY INDICATIONS

DIRECTIONS FOR USE

Mix Directions: If not using an automated pump system, then mix according to the following directions.

1. Measure one part of Express 1 Concentrate component into a clean empty, non-metallic container.

2. Add 20 parts cool potable water (at or below 77°F/25°C.)

3. Add one part Express 3 Concentrate component and mix.

4. This mixed solution Express 1 & 3 RTU (ready-to-use) will remain stable for 24 hours. After 24 hours discard any remaining solution and mix a new solution.

IMPORTANT: Do not add mixed Express 1 & 3 RTU ready-to-use to any other teat dip or other products. If transferred from this container to any other, make sure the other container is thoroughly pre-cleaned and bears the proper container labeling for Express 1 & 3 RTU.

Use of a complete cow-care program including both pre and post dipping may aid in reducing the spread of organisms which may cause mastitis.

DIRECTIONS FOR TEAT DIPPING

Pre-Milking: Fill teat dip cup with Express 1 & 3 RTU. Before each cow is milked, dip the teats as far as possible into the teat dip cup containing Express 1 & 3 RTU. Wipe teats dry after dipping, using single-service towels to avoid contamination of milk.

Udder and teats which are heavily soiled should be washed before using a pre-milking teat dip. Teats should be dried with a single-service towel and dipped in Express 1 & 3 RTU, wiping teats dry before milking.

Post-Milking: Immediately after milking, use Express 1 & 3 RTU at full strength. Submerge teat 2/3 their length in Express 1 & 3 RTU teat dip. Allow to air dry. Do not wipe. Always use fresh full strength Express 1 & 3 RTU. If product in dip cup becomes visibly dirty, discard contents and replenish with fresh product. Do not reuse or return unused product to the original container.

Do not turn cows into freezing weather until Express 1 & 3 RTU is completely dry.

NOTE: Express 1 & 3 RTU is not intended to cure or help in the healing of chapped or irritated teats. In case of irritation or chapping, have the condition examined and, if necessary, treated by a veterinarian.

OTHER SAFETY INFORMATION

IF SWALLOWED: Rinse mouth. Do NOT induce vomiting.

IF ON SKIN (or hair): Remove/ Take off immediately all contaminated clothing. Rinse skin with water/ shower. IF INHALED: Remove person to fresh air and keep comfortable for breathing. Immediately call a POISON CENTER/doctor. IF IN EYES: Rinse cautiously with water for several minutes. Remove contact lenses, if present and easy to do. Continue rinsing. Immediately call a POISON CENTER/doctor. Wash contaminated clothing before reuse.

READ SAFETY DATA SHEET (SDS) BEFORE USING THIS PRODUCT

EMERGENCY HEALTH INFORMATION: 1 800 328 0026. If located outside the United States and Canada, call collect 1 651 222 5352 (number is in the US).

Representative label and principal display panel

Express 3 Concentrate

Valiant quality milk system

ABS

Unique Teat Dip Concentrate Component

DO NOT MIX EXPRESS 1 AND EXPRESS 3 DIRECTLY TOGETHER

When properly mixed with potable water and Express 1, this solution is an aid in reducing the spread of organisms which may cause mastitis.

ACTIVE INGREDIENT:

Stabilized Sodium Salt of Chlorus Acid.............................................................3.65%

INERT INGREDIENTS:.............................................................................. 96.35%

TOTAL:.......................................................................................................100.00%

6300625

208 L (55 US GAL)

Distributed by:

ABS Global, Inc. ∙ P.O. Box 459

DeForest, Wisconsin USA 53532

www.absglobal.com

Manufactured by:

Ecolab Inc. ∙ 1 Ecolab Place ∙

St. Paul, MN 55102 USA ∙

tel: 1 800 392 3392

© 2018 Ecolab USA Inc ∙ All rights reserved

Made in U.S.A.

www.ecolab.com ∙ 753675/5302/1118